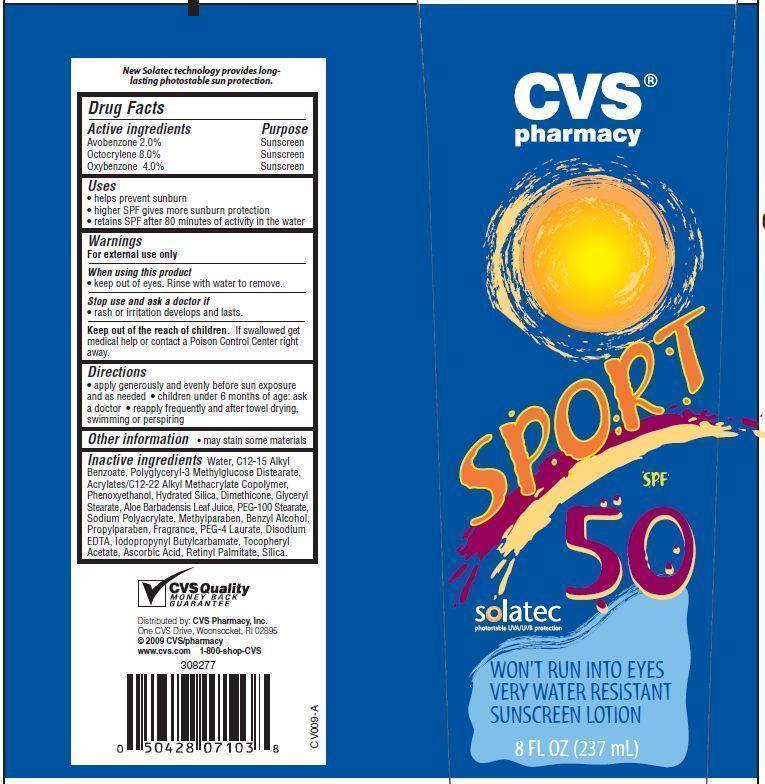 DRUG LABEL: CVS Pharmacy Sport SPF 50
NDC: 59779-017 | Form: LOTION
Manufacturer: CVS Pharmacy
Category: otc | Type: HUMAN OTC DRUG LABEL
Date: 20121218

ACTIVE INGREDIENTS: AVOBENZONE 2 g/100 g; OCTOCRYLENE 8 g/100 g; OXYBENZONE 4 g/100 g
INACTIVE INGREDIENTS: WATER; PHENOXYETHANOL; HYDRATED SILICA; DIMETHICONE; GLYCERYL MONOSTEARATE; ALOE VERA LEAF; PEG-100 STEARATE; METHYLPARABEN; BENZYL ALCOHOL; PROPYLPARABEN; PEG-4 LAURATE; EDETATE DISODIUM; .ALPHA.-TOCOPHEROL ACETATE; ASCORBIC ACID; VITAMIN A PALMITATE; SILICON DIOXIDE

Drug Facts

Active Ingredients

Avobenzone 2.0%
Octocrylene 8.0%
Oxybenzone 4.0%

Purpose

Sunscreen

Uses

- helps prevent sunburn
- higher SPF gives more sunburn protection
- retains SPF after 80 minutes of activity in the water

Warnings

For external use only

When using this product

- keep out of eyes.Rinse with water to remove.

Stop use and ask a doctor if

rash or irritation develops and lasts.

Keep out of the reach of children.

If swallowed get medical help or contact a Poison Control Center right away.

Directions

- apply generously and evenly before sun exposure and as needed
- Children under 6 months of age:ask a doctor
- reapply after towel drying, swimming or perspiring

Other Information

- May stain some materials

Inactive Ingredients

Water, C12-15 Alkyl Benzoate, Polyglyceryl-3 Methylglucose Distearate, Acrylates/C12-22 Alkyl Methacrylate Copolymer, Hydrated Silica, Glyceryl Stearate, Dimethicone, PEG-100 Stearate, Sodium Polyacrylate, Benzyl Alcohol, Disodium EDTA, PEG-4 Dilaurate, PEG-4 Laurate, PEG-4, PEG-8 Dimethicone, Aloe Barbadensis Leaf Juice Powder, Octyldodecanol, Retinyl Palmitate, Silica, Tocopheryl Acetate, Ascorbic Acid, Sodium Propoxyhydroxypropyl Thiosulfate Silica, Phenoxyethanol, Methylparaben, Propylparaben, Iodopropynyl Butylcarbamate, Fragrance.

Principal Display Panel

CVS
pharmacy
SPORT
SPF 50
solatec
photostable UVA/UVB protection
WON'T RUN INTO EYES
VERY WATER RESISTANT
SUNSCREEN LOTION
8 FL OZ (237 mL)